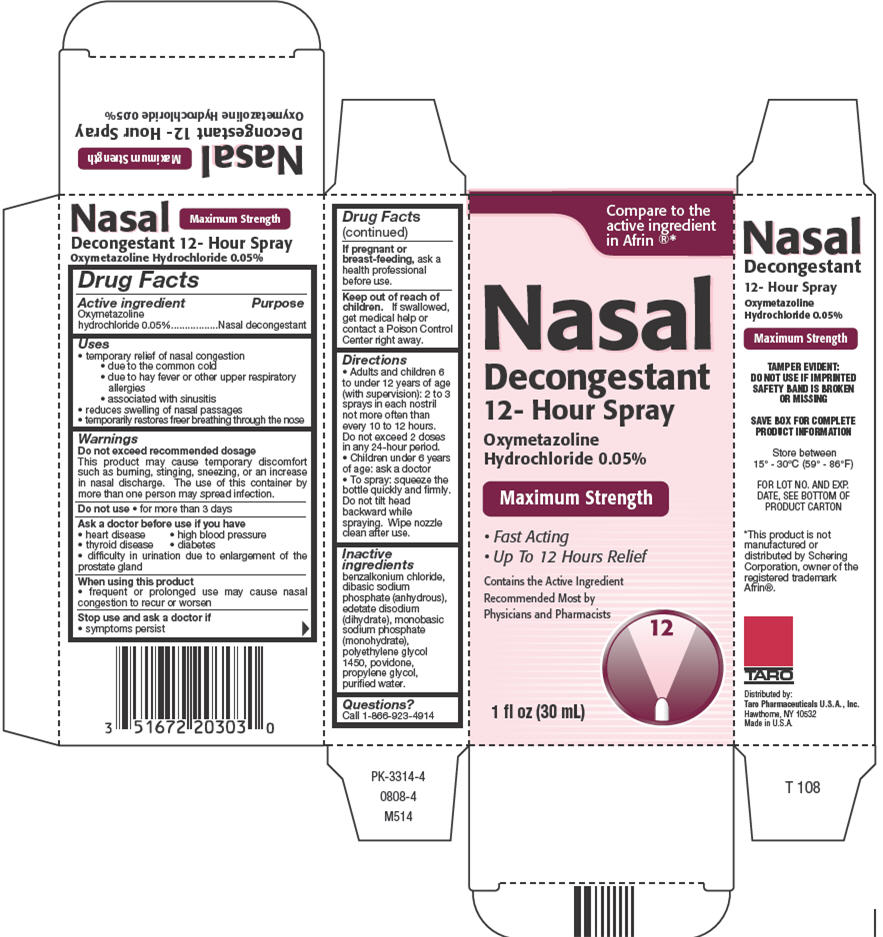 DRUG LABEL: Oxymetazoline Hydrochloride
NDC: 51672-2030 | Form: SPRAY
Manufacturer: Taro Pharmaceuticals U.S.A., Inc.
Category: otc | Type: HUMAN OTC DRUG LABEL
Date: 20250313

ACTIVE INGREDIENTS: OXYMETAZOLINE HYDROCHLORIDE 0.05 g/100 mL
INACTIVE INGREDIENTS: BENZALKONIUM CHLORIDE; SODIUM PHOSPHATE, DIBASIC, ANHYDROUS; EDETATE DISODIUM; SODIUM PHOSPHATE, MONOBASIC, MONOHYDRATE; POLYETHYLENE GLYCOL 1450; POVIDONE, UNSPECIFIED; PROPYLENE GLYCOL; WATER

Oxymetazoline Hydrochloride
Nasal Decongestant 12-Hour Spray

Drug Facts

Active ingredient

Oxymetazoline hydrochloride 0.05%

Purpose

Nasal decongestant

Uses

- temporary relief of nasal congestion
  - due to the common cold
  - due to hay fever or other upper respiratory allergies
  - associated with sinusitis
- reduces swelling of nasal passages
- temporarily restores freer breathing through the nose

Warnings

Do not exceed recommended dosage

This product may cause temporary discomfort such as burning, stinging, sneezing, or an increase in nasal discharge. The use of this container by more than one person may spread infection.

Do not use

- for more than 3 days

Ask a doctor before use if you have

- heart disease
- high blood pressure
- thyroid disease
- diabetes
- difficulty in urination due to enlargement of the prostate gland

When using this product

- frequent or prolonged use may cause nasal congestion to recur or worsen

Stop use and ask a doctor if

- symptoms persist

PREGNANCY OR BREAST FEEDING

If pregnant or breast-feeding,ask a health professional before use.

Keep out of reach of children.If swallowed, get medical help or contact a Poison Control Center right away.

Directions

- Adults and children 6 to under 12 years of age (with supervision): 2 to 3 sprays in each nostril not more often than every 10 to 12 hours. Do not exceed 2 doses in any 24-hour period.
- Children under 6 years of age: ask a doctor
- To spray: squeeze the bottle quickly and firmly. Do not tilt head backward while spraying. Wipe nozzle clean after use.

Inactive ingredients

benzalkonium chloride, dibasic sodium phosphate (anhydrous), edetate disodium (dihydrate), monobasic sodium phosphate (monohydrate), polyethylene glycol 1450, povidone, propylene glycol, purified water.

Questions?

Call 1-866-923-4914

Distributed by:
Taro Pharmaceuticals U.S.A., Inc.
Hawthorne, NY 10532

PRINCIPAL DISPLAY PANEL - 30 mL Bottle Carton

Compare to the
active ingredient
in Afrin®*

Nasal
Decongestant
12- Hour Spray

Oxymetazoline
Hydrochloride 0.05%

Maximum Strength

- Fast Acting
- Up To 12 Hours Relief

Contains the Active Ingredient
Recommended Most by
Physicians and Pharmacists

12

1 fl oz (30 mL)